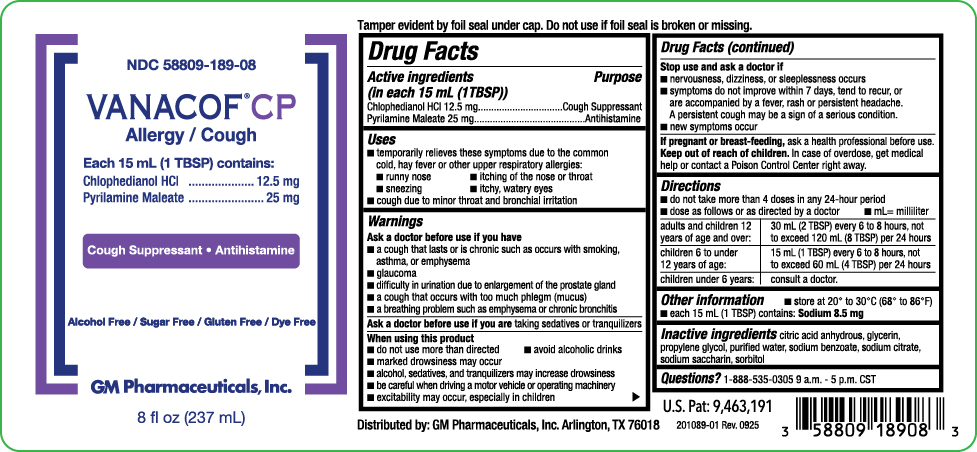 DRUG LABEL: VANACOF CP Allergy / Cough
NDC: 58809-189 | Form: SOLUTION
Manufacturer: GM Pharmaceuticals, INC
Category: otc | Type: HUMAN OTC DRUG LABEL
Date: 20251014

ACTIVE INGREDIENTS: CHLOPHEDIANOL HYDROCHLORIDE 12.5 mg/15 mL; PYRILAMINE MALEATE 25 mg/15 mL
INACTIVE INGREDIENTS: SODIUM CITRATE; SODIUM BENZOATE; PROPYLENE GLYCOL; WATER; SORBITOL; GLYCERIN; ANHYDROUS CITRIC ACID; SACCHARIN SODIUM

VANACOF CP Allergy / Cough

Active Ingredients (in each 15 mL (1TBSP))

Chlophedianol HCl 12.5 mg

Pyrilamine Maleate 25 mg

Purpose

Cough Suppressant

Antihistamine

Uses

■ temporarily relieves these symptoms due to the common cold, hay fever or other upper respiratory allergies:
■ runny nose ■ itching of the nose or throat
■ sneezing ■ itchy, watery eyes
■ cough due to minor throat and bronchial irritation

Warnings

Ask a doctor before use if you have

■ a cough that lasts or is chronic such as occurs with smoking, asthma, or emphysema
■ glaucoma
■ difficulty in urination due to enlargement of the prostate gland
■ a cough that occurs with too much phlegm (mucus)
■ a breathing problem such as emphysema or chronic bronchitis

Ask a doctor before use if you are

taking sedatives or tranquilizers

When using this product

■ do not use more than directed ■ avoid alcoholic drinks
■ marked drowsiness may occur
■ alcohol, sedatives, and tranquilizers may increase drowsiness
■ be careful when driving a motor vehicle or operating machinery
■ excitability may occur, especially in children

Stop use and ask a doctor if

■ nervousness, dizziness, or sleeplessness occurs
■ symptoms do not improve within 7 days, tend to recur, or are accompanied by a fever, rash or persistent headache. A persistent cough may be a sign of a serious condition.
■ new symptoms occur

If pregnant or breast-feeding,

ask a health professional before use.

Keep out of reach of children.

In case of overdose, get medical help or contact a Poison Control Center right away.

Directions

■ do not take more than 4 doses in any 24-hour period
■ dose as follows or as directed by a doctor ■ mL= milliliter

adults and children 12 years of age and over: | 30 mL (2 TBSP) every 6 to 8 hours, not to exceed 120 mL (8 TBSP) per 24 hours
children 6 to under 12 years of age: | 15 mL (1 TBSP) every 6 to 8 hours, not to exceed 60 mL (4 TBSP) per 24 hours
children under 6 years: | consult a doctor.

Other information

■ store at 20° to 30°C (68° to 86°F)
■ each 15 mL (1 TBSP) contains: Sodium 8.5 mg

Inactive ingredients

citric acid anhydrous, glycerin, propylene glycol, purified water, sodium benzoate, sodium citrate, sodium saccharin, sorbitol

Questions?

1-888-535-0305 9 a.m. - 5 p.m. CST

OTHER SAFETY INFORMATION

Tamper evident by foil seal under cap. Do not use if foil seal is broken or missing.

U.S. Pat: 9,463,191

Distributed by: GM Pharmaceuticals, Inc. Arlington, TX 76018

PACKAGE LABEL

NDC 58809-189-08

VANACOF®CP

Allergy / Cough

Each 15 mL (1 TBSP) contains:

Chlophedianol HCl .................... 12.5 mg

Pyrilamine Maleate ....................... 25 mg

Cough Suppressant • Antihistamine

Alcohol Free / Sugar Free / Gluten Free / Dye Free

GM Pharmaceuticals, Inc.

8 fl oz (237 mL)